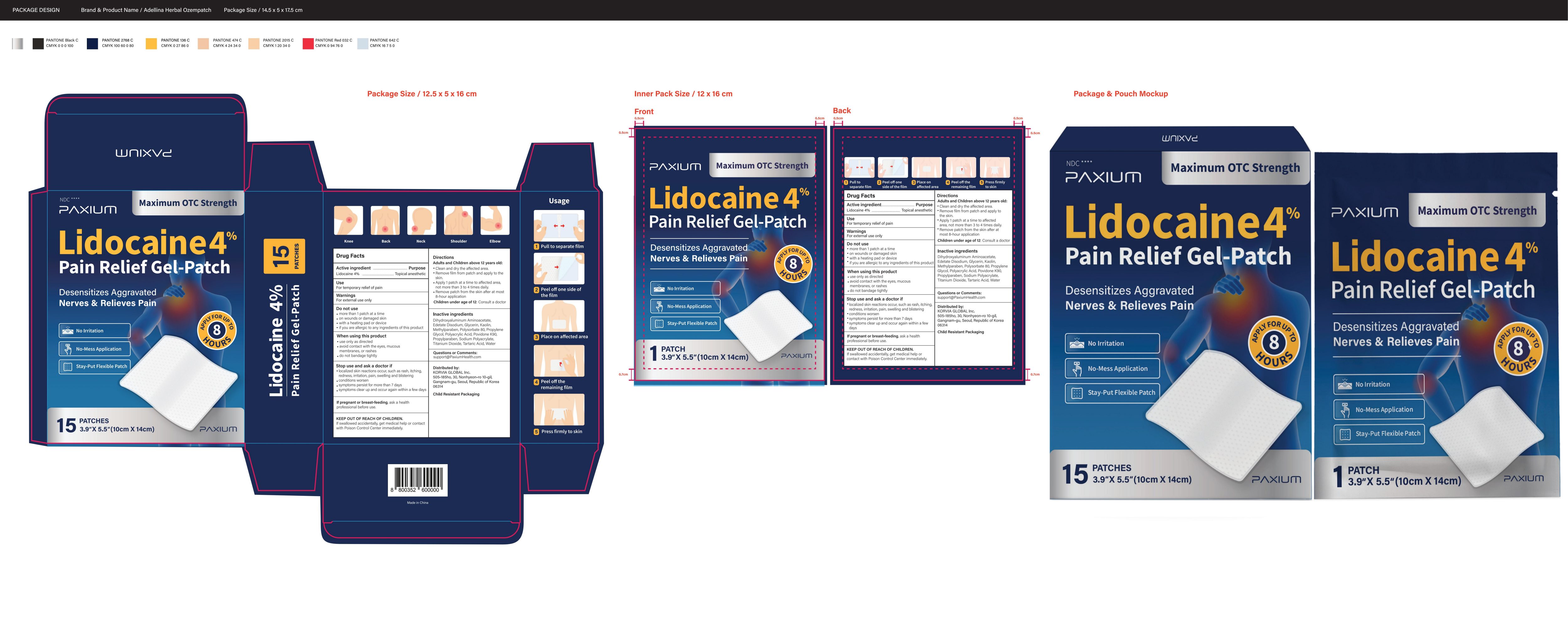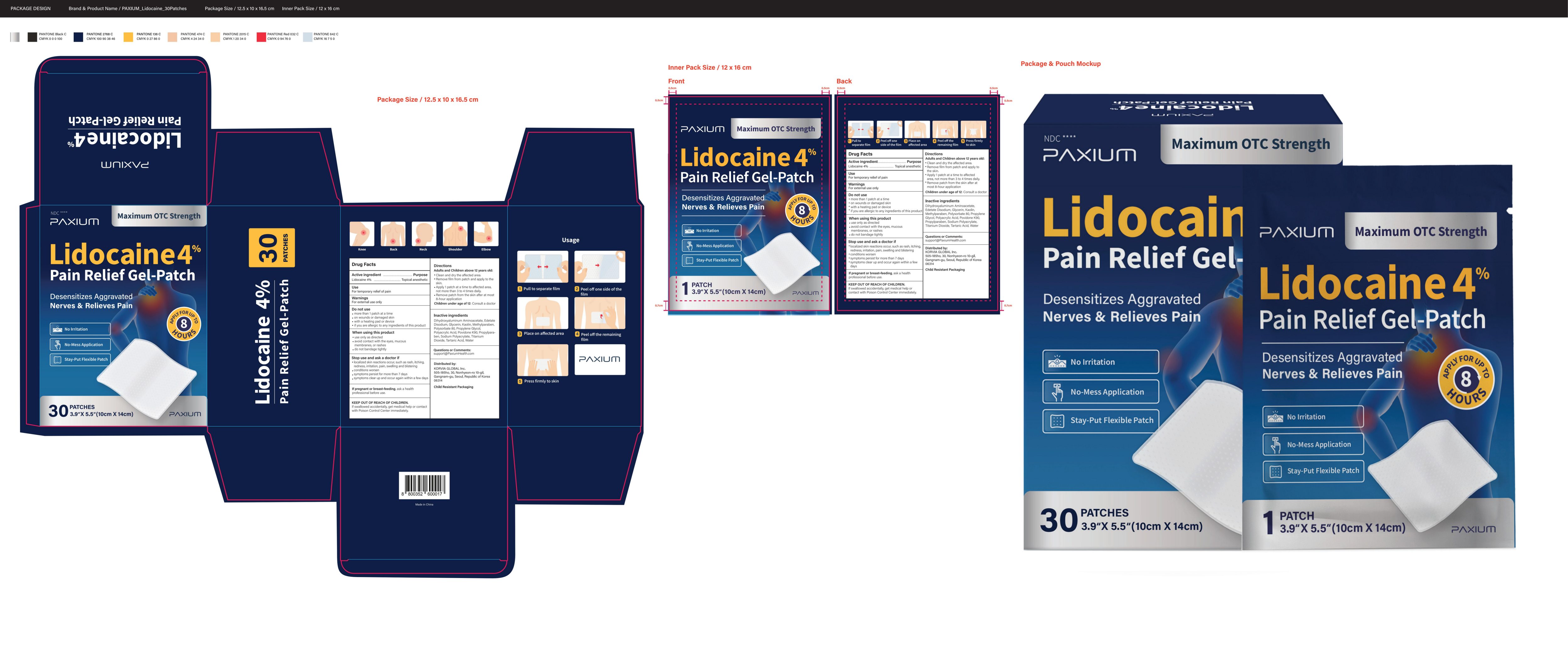 DRUG LABEL: Pain Relief Gel-Patch
NDC: 87253-187 | Form: PATCH
Manufacturer: KORVIA GLOBAL Inc.
Category: otc | Type: HUMAN OTC DRUG LABEL
Date: 20251212

ACTIVE INGREDIENTS: LIDOCAINE 0.04 g/1 g
INACTIVE INGREDIENTS: POLYSORBATE 80; GLYCERIN; POVIDONE K90; METHYLPARABEN; PROPYLPARABEN; EDETATE DISODIUM; KAOLIN; TARTARIC ACID; WATER; PROPYLENE GLYCOL; POLYACRYLIC ACID (250000 MW); SODIUM POLYACRYLATE (2500000 MW); TITANIUM DIOXIDE; DIHYDROXYALUMINUM AMINOACETATE ANHYDROUS

87253-187

Active ingredient

Lidocaine 4% ...... Purpose: Topical Anesthetic

Purpose

Topical Anesthetic

Uses

For temporary relief of pain

Warnings

For external use only

Ask a doctor if:

- localized skin reactions occur, such as rash, itching, redness, irritation, pain, swelling and blistering
- Conditions worsen
- Symptoms persists for more than 7 days
- Symptoms clear up and occur again within a few days

When using this product

- Use only as directed
- Avoid contact with the eyes, mucous membranes or rashes
- Do not bandage tightly

Do not use

- More than 1 patch at a time
- On wounds or damaged skin
- with a heating pad or device
- If you are allergic to any ingredients of this product

Stop use if:

- localized skin reactions occur, such as rash, itching, redness, irritation, pain, swelling and blistering
- Conditions worsen
- Symptoms persists for more than 7 days
- Symptoms clear up and occur again within a few days

Pregnancy or breast feeding

If pregnant or breast-feeding, ask a health professional before use

Keep out of reach of children. If swallowed accidentally, get medical help or contact with Poison Control Center immediately.

Directions

Adult and Children 12 years of age and over:

- Clean and dry the affected area
- Remove film from patch and apply to the skin
- Apply 1 patch at a time to affected area, not more than 3 to 4 times daily
- Remove patch from the skin after at most 8-hour application

Children under 12 years of age: Consult a doctor

Questions or Comments?

support@PaxiumHealth.com

Inactive ingredients

Dihydroxyaluminum Aminoacetate, Edetate Disodium,Glycerin, Kaolin, Methylparaben, Polysorbate 80,Propylene Glycol, Polyacrylic Acid, Povidone K90,Propylparaben, Sodium Polyacrylate, Tartaric Acid,Titanium Dioxide, Water.